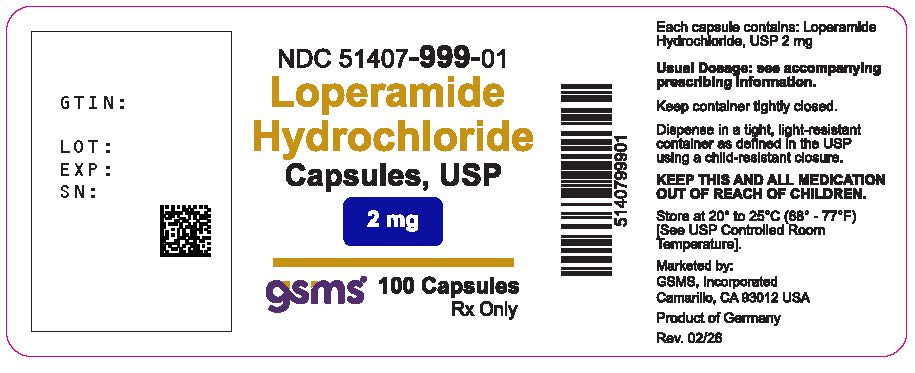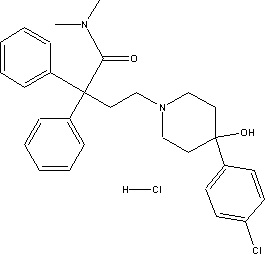 DRUG LABEL: Loperamide Hydrochloride
NDC: 51407-999 | Form: CAPSULE
Manufacturer: Golden State Medical Supply, Inc.
Category: prescription | Type: HUMAN PRESCRIPTION DRUG LABEL
Date: 20260224

ACTIVE INGREDIENTS: LOPERAMIDE HYDROCHLORIDE 2 mg/1 1
INACTIVE INGREDIENTS: LACTOSE MONOHYDRATE; SODIUM STARCH GLYCOLATE TYPE A POTATO; SILICON DIOXIDE; MAGNESIUM STEARATE; GELATIN; TITANIUM DIOXIDE; FERRIC OXIDE YELLOW; FERRIC OXIDE RED; FERROSOFERRIC OXIDE; PROPYLENE GLYCOL; SHELLAC; POTASSIUM HYDROXIDE; CELLULOSE, MICROCRYSTALLINE

Loperamide Hydrochloride

BOXED WARNING

WARNING: TORSADES DE POINTES AND SUDDEN DEATH

- Cases of Torsades de Pointes, cardiac arrest, and death have been reported with the use of a higher than recommended dosages of Loperamide Hydrochloride Capsules (see WARNINGS and OVERDOSAGE).

- Loperamide Hydrochloride Capsules is contraindicated in pediatric patients less than 2 years of age (see CONTRAINDICATIONS).
- Avoid Loperamide Hydrochloride Capsules dosages higher than recommended in adults and pediatric patients 2 years of age and older due to the risk of serious cardiac adverse reactions (see DOSAGE AND ADMINISTRATION).

DESCRIPTION

Loperamide Hydrochloride Capsules USP (loperamide hydrochloride), 4-(p-chlorophenyl)-4-hydroxy-N,N-dimethyl- a,a-diphenyl-1-piperidinebutyramide monohydrochloride, is a synthetic antidiarrheal for oral use.

Loperamide Hydrochloride Capsules USP is available in 2mg capsules.

The inactive ingredients are: Magnesium stearate, microcrystalline cellulose, sodium starch glycolate, lactose monohydrate, colloidal silicon dioxide. In addition, the hard gelatin capsule also contains gelatin, black iron oxide, red iron oxide, titanium dioxide and yellow iron oxide. The black printing ink contains black iron oxide, propylene glycol, shellac, and potassium hydroxide.

CLINICAL PHARMACOLOGY

Mechanism of Action

In vitroand animal studies show that Loperamide Hydrochloride Capsules (loperamide hydrochloride) acts by slowing intestinal motility and by affecting water and electrolyte movement through the bowel.

Loperamide binds to the opiate receptor in the gut wall. Consequently, it inhibits the release of acetylcholine and prostaglandins, thereby reducing propulsive peristalsis, and increasing intestinal transit time. Loperamide increases the tone of the anal sphincter, thereby reducing incontinence and urgency.

Pharmacodynamics

Loperamide prolongs the transit time of the intestinal contents. It reduces daily fecal volume, increases the viscosity and bulk density, and diminishes the loss of fluid and electrolytes.

Tolerance to the antidiarrheal effect has not been observed.

Pharmacokinetics

Absorption

Plasma concentrations of unchanged drug remain below 2 ng/mL after the intake of a 2 mg capsule of Loperamide Hydrochloride Capsules. Plasma loperamide concentrations are highest approximately 5 hours after administration of the capsule and 2.5 hours after the liquid. The peak plasma concentrations of loperamide were similar for both formulations.

Distribution

Based on literature information, the plasma protein binding of loperamide is about 95%. Loperamide is a P-glycoprotein substrate.

Elimination

The apparent elimination half-life of loperamide is 10.8 hours with a range of 9.1 to 14.4 hours. Elimination of loperamide mainly occurs by oxidative N-demethylation.

Metabolism

In vitroloperamide is metabolized mainly by cytochrome P450 (CYP450) isozymes, CYP2C8 and CYP3A4, to form- N-demethyl loperamide. In an invitro study quercetin (CYP2C8 inhibitor) and ketoconazole (CYP3A4 inhibitor) significantly inhibited the N-demethylation process by 40% and 90%, respectively. In addition, CYP2B6 and CYP2D6 appear to play a minor role in loperamide N-demethylation.

Concomitant use of Loperamide Hydrochloride Capsules with inhibitors of CYP3A4 (e.g., itraconazole) or CYP2C8 (e.g., gemfibrozil) or inhibitors of P-glycoprotein (e.g., quinidine, ritonavir) can increase exposure to loperamide (see PRECAUTIONS, Drug Interactions).

Excretion

Excretion of the unchanged loperamide and its metabolites mainly occurs through the feces.

INDICATIONS & USAGE

Loperamide Hydrochloride Capsules (loperamide hydrochloride) is indicated for the control and symptomatic relief of acute nonspecific diarrhea in patients 2 years of age and older and of chronic diarrhea in adults associated with inflammatory bowel disease. Loperamide Hydrochloride Capsules is also indicated for reducing the volume of discharge from ileostomies.

CONTRAINDICATIONS

Loperamide Hydrochloride Capsules is contraindicated in:

- pediatric patients less than 2 years of age due to the risks of respiratory depression and serious cardiac adverse reactions (see WARNINGS).
- patients with a known hypersensitivity to loperamide hydrochloride or to any of the excipients.
- patients with abdominal pain in the absence of diarrhea.
- patients with acute dysentery, which is characterized by blood in stools and high fever.
- patients with acute ulcerative colitis.
- patients with bacterial enterocolitis caused by invasive organisms including Salmonella, Shigella, and Campylobacter.
- patients with pseudomembranous colitis (e.g., Clostridium difficle) associated with the use of broad-spectrum antibiotics.

WARNINGS

Cardiac Adverse Reactions, Including Torsades de Pointes and Sudden DeathCases of prolongation of the QT/QTc interval, Torsades de Pointes, other ventricular arrhythmias, cardiac arrest, some resulting in death, have been reported in adults with use of higher than recommended doses per day of Loperamide Hydrochloride Capsules Cases include patients who were abusing or misusing loperamide hydrochloride (see OVERDOSAGEand DRUG ABUSE AND DEPENDENCE). Cases of syncope and ventricular tachycardia have been reported in adult patients receiving the recommended dosage of Loperamide Hydrochloride Capsules. Some of these patients were taking other drugs or had other risk factors that may have increased their risk of cardiac adverse reactions. Additionally, postmarketing cases of cardiac arrest, syncope, and respiratory depression have been reported in pediatric patients less than 2 years of age.

Loperamide Hydrochloride Capsules is contraindicated in pediatric patients less than 2 years of age due to the risks of respiratory depression and serious cardiac adverse reactions. Avoid Loperamide Hydrochloride Capsules dosages higher than recommended in adults and pediatric patients 2 years of age and older due to the risk of serious cardiac adverse reactions (see DOSAGE AND ADMINISTRATION, OVERDOSAGE)

Avoid Loperamide Hydrochloride Capsules in:

- combination with others drugs or herbal products that are known to prolong the QT interval, including Class 1A (e.g., quinidine, procainamide) or Class III (e.g., amiodarone, sotalol) antiarrhythmics, antipsychotics (e.g., chlorpromazine, haloperidol, thioridazine, ziprasidone), antibiotics (e.g., moxifloxacin), or any other drug known to prolong the QT interval (e.g., pentamidine, levomethadyl acetate, methadone)
- patients with risk factors for QT prolongation, including patients with congenital long QT syndrome, with a history of cardiac arrhythmias or other cardiac conditions, elderly patients and those with electrolyte abnormalities.

Dehydration

Fluid and electrolyte depletion often occur in patients who have diarrhea. In such cases, administration of appropriate fluid and electrolytes is very important. The use of Loperamide Hydrochloride Capsules does not preclude the need for appropriate fluid and electrolyte therapy.

Gastrointestinal Disorders

In general, Loperamide Hydrochloride Capsules should not be used when inhibition of peristalsis is to be avoided due to the possible risk of significant sequelae including ileus, megacolon and toxic megacolon.

Loperamide Hydrochloride Capsules must be discontinued promptly when constipation, abdominal distention or ileus develop.

Treatment of diarrhea with Loperamide Hydrochloride Capsules is only symptomatic. Whenever an underlying etiology can be determined, specific treatment should be given when appropriate (or when indicated).

Patients with AIDS treated with Loperamide Hydrochloride Capsules, 2 mg for diarrhea should have therapy stopped at the earliest signs of abdominal distention. There have been isolated reports of toxic megacolon in AIDS patients with infectious colitis from both viral and bacterial pathogens treated with loperamide hydrochloride.

Variability in Pediatric Response

Loperamide Hydrochloride Capsules should be used with special caution in pediatric patients because of the greater variability of response in this age group. Dehydration, particularly in pediatric patients less than 6 years of age, may further influence the variability of response to Loperamide Hydrochloride Capsules. Loperamide Hydrochloride Capsules is contraindicated in pediatric patients less than 2 years of age due to the risks of respiratory depression and serious cardiac adverse reactions.

PRECAUTIONS

GENERAL PRECAUTIONS

Allergic Reactions

Extremely rare allergic reactions including anaphylaxis and anaphylactic shock have been reported.

Hepatic Impairment

The effects of hepatic impairment on the pharmacokinetics of loperamide have not been studied. Use Loperamide Hydrochloride Capsules with caution in such patients because the systemic exposure to loperamide may be increased due to reduced metabolism. Monitor patients with hepatic impairment closely for signs of central nervous system (CNS) toxicity.

Renal Impairment

No pharmacokinetic data are available in patients with renal impairment. Since it has been reported that the majority of the drug is metabolized and metabolites or the unchanged drug are excreted mainly in the feces, dosage adjustments in patients with renal impairment are not required.

Geriatric Use

No formal studies have been conducted to evaluate the pharmacokinetics of loperamide in elderly subjects. However, in two studies that enrolled elderly patients, there were no major differences in the drug disposition in elderly patients with diarrhea relative to young patients.

In general, elderly patients may be more susceptible to drug-associated effects on the QT interval. Avoid Loperamide Hydrochloride Capsules in elderly patients taking drugs that can result in prolongation of the QT interval (for example, Class IA or III antiarrhythmics) or in patients with risk factors for Torsades de Pointes (see WARNINGS).

INFORMATION FOR PATIENTS

Advise patients:

- to take Loperamide Hydrochloride Capsules at the prescribed dosage. Use of a higher than prescribed dosage is not recommended (see WARNINGS). Report to a healthcare facility if you or someone you are caring for taking Loperamide Hydrochloride Capsules experiences fainting episode, a rapid or irregular heartbeat or become unresponsive.
- with acute diarrhea, that if clinical improvement is not observed in 48 hours, discontinue Loperamide Hydrochloride Capsules and contact their healthcare provider.
- to contact their healthcare provider if they see blood in their stools, or if they develop a fever or abdominal distention.

- to use caution when driving a car or operating machinery, as tiredness, dizziness, or drowsiness may occur in the setting of diarrheal syndromes treated with Loperamide Hydrochloride Capsules. (see ADVERSE REACTIONS)
  to tell their healthcare provider about all the medications they are taking, including prescription and over-the-counter medications, vitamins and herbal supplements, especially if they take Class 1A (e.g., quinidine, procainamide) or Class III (e.g., amiodarone, sotalol) antiarrhythmics, antipsychotics (e.g., chlorpromazine, haloperidol, thioridazine, ziprasidone), antibiotics (e.g., moxifloxacin), or any other drug known to prolong the QT interval (e.g., pentamidine, levomethadyl acetate, methadone).

DRUG INTERACTIONS

Effects of Other Drugs on Loperamide

Concomitant use of Loperamide Hydrochloride Capsules with inhibitors of CYP3A4 (e.g., itraconazole) or CYP2C8 (e.g., gemfibrozil) or inhibitors of P-glycoprotein (e.g., quinidine, ritonavir) can increase exposure to loperamide. The increased systemic exposure to loperamide may increase a risk for cardiac adverse reactions especially in patients who are taking multiple CYP enzyme inhibitors, or in patients with underlying cardiac conditions (see WARNINGS). Monitor patients for cardiac adverse reactions.

CYP3A4 Inhibitors

Itraconazole

Concomitant administration of multiple doses of 100 mg itraconazole twice daily, an inhibitor of both CYP3A4 and P-glycoprotein, with a single 4-mg dose of loperamide hydrochloride increased the peak plasma concentration and the systemic exposure to loperamide by 2.9-fold and 3.8-fold, respectively.

CYP2C8 Inhibitors

Gemfibrozil

When a single 4-mg dose of loperamide hydrochloride was co-administered with 600 mg gemfibrozil, a strong inhibitor of CYP2C8, on day 3 of a 5-day treatment with gemfibrozil twice daily, the mean peak plasma concentration and the systemic exposure to loperamide was increased by 1.6-fold and 2.2-fold, respectively.

CYP3A4 and CYP2C8 Inhibitors

When multiple doses of both 100 mg itraconazole and 600 mg gemfibrozil twice daily were administered with a single 4-mg dose of loperamide hydrochloride, the mean peak plasma concentration and the systemic exposure to loperamide was increased by 4.2-fold and 12.6-fold, respectively.

P-glycoprotein Inhibitors

Concomitant administration of a 16 mg single dose of loperamide hydrochloride with a 600 mg single dose of quinidine or ritonavir, both of which are P-glycoprotein inhibitors, resulted in a 2- to 3-fold increase in loperamide plasma concentrations. Due to the potential for enhanced CNS adverse reactions when loperamide is co-administered with quinidine and with ritonavir, caution should be exercised when Loperamide Hydrochloride Capsules USP, 2 mg is administered at the recommended dosages (2 mg, up to 16 mg maximum daily dose) with P-glycoprotein inhibitors.

Effects of Loperamide on Other Drugs

Saquinavir

When a single 16-mg dose of loperamide hydrochloride is coadministered with a 600 mg single dose of saquinavir, loperamide decreased saquinavir exposure by 54%, which may be of clinical relevance due to reduction of therapeutic efficacy of saquinavir. The effect of saquinavir on loperamide is of less clinical significance. Therefore, when Loperamide Hydrochloride Capsules is given with saquinavir, the therapeutic efficacy of saquinavir should be closely monitored.

CARCINOGENESIS & MUTAGENESIS & IMPAIRMENT OF FERTILITY

In an 18-month rat study with oral loperamide hydrochloride doses up to 40 mg/kg/day (21 times the maximum human dose of 16 mg/day, based on a body surface area comparison), there was no evidence of carcinogenesis.

Loperamide was not genotoxic in the Ames test, the SOS chromotest in E. coli,the dominant lethal test in female mice, or the mouse embryo cell transformation assay.

Fertility and reproductive performance was evaluated in rats using oral doses of 2.5, 10, and 40 mg/kg/day (females only) in a second study. Oral administration of 20 mg/kg/day (approximately 11 times the human dose based on a body surface area comparison) and higher, produced a strong impairment of female fertility. Treatment of female rats with up to 10 mg/kg/day (approximately 5 times the human dose based on a body surface area comparison) had no effect on fertility. Treatment of male rats with oral doses of 40 mg/kg/day (approximately 21 times the human dose based on a body surface area comparison) produced impairment of male fertility, whereas administration of up to 10 mg/kg/day (approximately 5 times the human dose based on a body surface area comparison) had no effect.

PREGNANCY

Teratogenic Effects

Teratology studies have been performed in rats using oral loperamide hydrochloride doses of 2.5, 10, and 40 mg/kg/day, and in rabbits using oral doses of 5, 20, and 40 mg/kg/day. These studies have revealed no evidence of impaired fertility or harm to the fetus at doses up to 10 mg/kg/day in rats (5 times the human dose based on body surface area comparison) and 40 mg/kg/day in rabbits (43 times the human dose based on body surface area comparison). Treatment of rats with oral doses of 40 mg/kg/day (21 times the human dose based on a body surface area comparison) produced marked impairment of fertility. The studies produced no evidence of teratogenic activity. There are no adequate and well controlled studies in pregnant women. Loperamide Hydrochloride Capsules should be used during pregnancy only if the potential benefit justifies the potential risk to the fetus.

Nonteratogenic Effects

In a peri- and post-natal development study in rats, oral administration of 40 mg/kg/day produced impairment of growth and survival of offspring.

NURSING MOTHERS

Small amounts of loperamide may appear in human breast milk. Therefore, Loperamide Hydrochloride Capsules is not recommended during breast-feeding.

PEDIATRIC USE

Loperamide Hydrochloride Capsules, 2 mg is contraindicated in pediatric patients less than 2 years of age due to the risks of respiratory depression and serious cardiac adverse reactions (see CONTRAINDICATIONS). Postmarketing cases of cardiac arrest, syncope, and respiratory depression have been reported in pediatric patients less than 2 years of age (see WARNINGS). Pediatric patients may be more sensitive to CNS effects, such as altered mental status, somnolence, and respiratory depression, than adults. There have been rare reports of paralytic ileus associated with

abdominal distention. Most of these reports occurred in the setting of acute dysentery, overdose, and with pediatric patients less than two years of age.

Loperamide Hydrochloride Capsules should be used with special caution in pediatric patients because of their greater variability of response (see WARNINGS). Dehydration, particularly in pediatric patients less than 6 years of age, may further influence the variability of response to Loperamide Hydrochloride Capsules

The safety and effectiveness of Loperamide Hydrochloride Capsules in pediatric patients with chronic diarrhea have not been established. Although Loperamide Hydrochloride Capsules has been studied in a limited number of pediatric patients with chronic diarrhea; the therapeutic dose for the treatment of chronic diarrhea in a pediatric population has not been established.

In case of accidental overdosage of Loperamide Hydrochloride Capsules by pediatric patients, see OVERDOSAGEfor suggested treatment.

ADVERSE REACTIONS

Clinical Trial Experience

The adverse effects reported during clinical investigations of Loperamide Hydrochloride Capsules (loperamide hydrochloride) are difficult to distinguish from symptoms associated with the diarrheal syndrome. Adverse experiences recorded during clinical studies with Loperamide Hydrochloride Capsules were generally of a minor and self-limiting nature. They were more commonly observed during the treatment of chronic diarrhea.

The adverse events reported are summarized irrespective of the causality assessment of the investigators.

1) Adverse events from 4 placebo-controlled studies in patients with acute diarrhea The adverse events with an incidence of 1.0% or greater, which were reported at least as often in patients on loperamide hydrochloride as on placebo, are presented in the table below.

 | Acute Diarrhea
 | Loperamide Hydrochloride | Placebo
No. of treated patients | 231 | 236
Gastrointestinal AE% Constipation | 2.6% | 0.8%

The adverse events with an incidence of 1.0% or greater, which were more frequently reported in patients on placebo than on loperamide hydrochloride, were: dry mouth, flatulence, abdominal cramp and colic.

2) Adverse events from 20 placebo-controlled studies in patients with chronic diarrhea The adverse events with an incidence of 1.0% or greater, which were reported at least as often in patients on loperamide hydrochloride as on placebo, are presented below in the table below.

 | Chronic Diarrhea
 | Loperamide Hydrochloride | Placebo
No. of treated patients | 285 | 277
Gastrointestinal AE% Constipation | 5.3% | 0.0%
Central and peripheral nervous system AE% Dizziness | 1.4% | 0.7%

The adverse events with an incidence of 1.0% or greater, which were more frequently reported in patients on placebo than on loperamide hydrochloride were: nausea, vomiting, headache, meteorism, abdominal pain, abdominal cramp and colic.

3) Adverse events from seventy-six controlled and uncontrolled studies in patients with acute or chronic diarrhea The adverse events with an incidence of 1.0% or greater in patients from all studies are given in the table below.

 | Acute Diarrhea | Chronic Diarrhea | All Studiesa
No. of treated patients | 1913 | 1371 | 3740
Gastrointestinal AE% Nausea Constipation Abdominal cramps | 0.7% 1.6% 0.5% | 3.2% 1.9% 3.0% | 1.8% 1.7% 1.4%

a. All patients in all studies, including those in which it was not specified if the adverse events occurred in patients with acute or chronic diarrhea.

Postmarketing Experience

The following adverse events have been reported:

Cardiac disorders

QT/QTc interval prolongation, Torsades de Pointes, other ventricular arrhythmias, cardiac arrest, syncope, and death (see WARNINGS, OVERDOSAGE).

Skin and subcutaneous tissue disorders

Rash, pruritus, urticaria, and angioedema and extremely rare cases bullous eruption including erythema multiforme, Stevens-Johnson syndrome and Toxic Epidermal Necrolysis have been reported with use of Loperamide Hydrochloride Capsules.

Immune system disorders

Isolated occurrences of allergic reactions and in some cases severe hypersensitivity reactions including anaphylactic shock and anaphylactoid reactions have been reported with the use of Loperamide Hydrochloride Capsules.

Gastrointestinal disorders

Dry mouth, abdominal pain, distention or discomfort, nausea, vomiting, flatulence, dyspepsia, constipation, paralytic ileus, megacolon; including toxic megacolon (see CONTRAINDICATIONS, WARNINGS).

Renal and urinary disorders

Urinary retention

Nervous system disorders

Drowsiness, dizziness

General disorders and administrative site conditions

Tiredness

A number of the adverse events reported during the clinical investigations and post-marketing experience with loperamide are frequent symptoms of the underlying diarrheal syndrome (abdominal pain/discomfort, nausea, vomiting, dry mouth, tiredness, drowsiness, dizziness, constipation, and flatulence). These symptoms are often difficult to distinguish from undesirable drug effects.

DRUG ABUSE AND DEPENDENCE

CONTROLLED SUBSTANCE

Loperamide is not a controlled substance.

ABUSE

Loperamide is a mu-opioid agonist. A human abuse potential study of loperamide hydrochloride at single doses up to 60 mg (3.75 times the recommended maximum adult dosage of 16 mg per day) was compared, in a double-blind cross-over design using nine subjects who had been active opiate users, to a threshold dose of codeine sulfate at 120 mg (96 mg base) or placebo. This resulted in one subject (11%) feeling a drug on placebo and identifying it as "dope" (heroin) and liking it slightly. Codeine was felt by 56% of subjects and identified as "dope" by 44%. Loperamide was felt by 44% of subjects and identified as "dope" by 11% and possibly dope mixed with some other kind of drug by another 22%. Loperamide abuse and misuse have been reported, especially at doses of 60 mg or greater. Loperamide can have greater CNS opioid effects at higher doses or with co-administration of drugs that increase systemic exposure and/or increase CNS penetration of loperamide (through inhibition of the CYP450 enzyme system or inhibition of P-glycoprotein). Loperamide is primarily being misused for relief from opioid withdrawal, and abused by a few users who obtain some (reportedly mild-moderate) level of euphoria.

DEPENDENCE

In animals, parenteral administration of loperamide hydrochloride can cause physical dependence, cross-tolerance to opioids, and all the other pharmacologic effects typical of mu- opioid agonists. Studies in morphine-dependent monkeys demonstrated that loperamide hydrochloride at doses above those recommended for humans prevented signs of morphine withdrawal.

OVERDOSAGE

The use of higher than recommended Loperamide Hydrochloride Capsules doses may result in life-threatening cardiac, CNS and respiratory adverse reactions.

If over-exposure occurs, call your Poison Control Center at 1-800-222-1222 for current information on the management of poisoning or overdosage.

Cardiac Effects

Symptoms

Cases of overdosage with loperamide hydrochloride (chronic ingestion of doses ranging from 70 mg to 1600 mg daily; 4 to 100 times the recommended dose) have resulted in life-threatening cardiac adverse reactions, including QT/QTc and QRS interval prolongation, Torsades de Pointes, Brugada syndrome and other ventricular arrhythmias, syncope, cardiac arrest, and death. Cases include patients who were abusing (using supratherapeutic doses in place of opioids to induce euphoria) or misusing (taking higher than recommended doses to control diarrhea or to prevent opioid withdrawal) loperamide. The following are representative cases that included cardiac adverse reactions:

- 25 year old abused loperamide and presented to the hospital on multiple occasions with symptoms of syncope, nausea, vomiting, bradycardia, hypotensive shock. The patient also experienced ventricular tachycardia, a prolonged QTc of 527 ms and QRS interval of 170 ms, frequent premature ventricular contractions, and subsequent cardiac arrest and death (elevated loperamide blood concentration of 32 ng/ml).
- 54 year old misused loperamide hydrochloride (up to 144 mg per day) as a self- treatment for chronic diarrhea for over 2 years. Signs of cardiac toxicity included syncope, prolonged QT of 500 ms sinus arrest with junctional escape rhythm, and polymorphic ventricular tachycardia, which required cardioversion and implantable cardioverter-defibrillator (ICD) management.
- 26 year old, with prior opioid abuse, presented to the hospital with recurrent syncope and developed Torsades de Pointes requiring electrical cardioversion. An ECG revealed a sinus rhythm with a heart rate of 85 bpm and a markedly prolonged QTc interval of greater than 700 ms. The patient reported ingesting 100 to 250 mg of loperamide hydrochloride with 400 mg of cimetidine daily for several months to simulate the euphoric sensation associated with opioids.

Management

Consider loperamide as a possible cause of cardiac arrhythmias in patients who may have a history of opioid abuse or recent ingestion of unknown drugs and in the differential diagnosis of unstable arrhythmias, prolonged QTc or QRS intervals, and Torsades de Pointes.

If loperamide-induced cardiac toxicity is suspected, promptly discontinue the drug and initiate therapy to manage and prevent cardiac arrhythmias and serious outcomes.

In many cases of loperamide overdosage, anti-arrhythmic medications (e.g., magnesium sulfate) were ineffective in resolving the arrhythmias and preventing further episodes of Torsades de Pointes. Electrical cardioversion and overdrive pacing, and isoproterenol continuous infusion were reported to manage QTc prolongation in the setting of overdose.

Laboratory Testing

Loperamide serum concentrations are not widely available or clinically useful to guide patient management.

CNS and Respiratory Depression

Symptoms

Cases of loperamide overdose (including relative overdose due to hepatic dysfunction), may cause opioid toxic effects including CNS depression (e.g. altered mental status, stupor, coordination disorders, somnolence, miosis, muscular hypertonia, respiratory depression), hypotension, urinary retention, and paralytic ileus. Pediatric patients may be more sensitive to CNS effects, including respiratory depression, than adults.

Management

Loperamide non-cardiac arrhythmia overdosages should be treated as opioid overdosages. Naloxone may reverse the opioid-related toxicity, including CNS and respiratory depression, and hypotension, associated with loperamide overdosage.

In adults and pediatric patients, naloxone may be administered intravenously. Appropriate doses of naloxone, via intranasal, intramuscular, intraosseous, or subcutaneous administration may be necessary if the intravenous route is not available. If the desired degree of opioid- related toxicity counteraction and improvement are not obtained, naloxone may be repeated at two- to three-minute intervals. If no response in opioid-related effects is observed after naloxone has been administered, then diagnosis of opioid-induced toxicity should be questioned.

Refer to the naloxone prescribing information for complete information on initial and subsequent dosages.

For patients whose adverse reactions are responsive to naloxone, monitor vital signs, neurologic and cardiopulmonary status for recurrence of opioid overdose symptoms for at least 24 hours after the last dose of naloxone, due to the prolonged intestinal retention of loperamide and the short duration (one to three hours) of naloxone. Patients with severe CNS or respiratory depression, and those who require multiple doses of naloxone to reverse symptoms, should be admitted to the hospital and may require intensive care.

Laboratory Testing

Standard drug screens for opioids do not include an assay for loperamide; such testing for opioids will yield negative results even in the presence of loperamide.

DOSAGE & ADMINISTRATION

Loperamide Hydrochloride Capsules is contraindicated in pediatric patients less than 2 years of age due to the risks of respiratory depression and serious cardiac adverse reactions (see CONTRAINDICATIONS).

Avoid Loperamide Hydrochloride Capsules dosages higher than recommended in adult or pediatric patients 2 years of age and older due to the risk of serious cardiac adverse reactions (See WARNINGS, OVERDOSAGE).

(1 capsule = 2 mg)

Patients should receive appropriate fluid and electrolyte replacement as needed.

Acute Diarrhea

Adults and Pediatric Patients 13 Years and Older:The recommended initial dose is 4mg (two capsules) followed by 2 mg (one capsule) after each unformed stool. The maximum daily dose is 16mg (eight capsules). Clinical improvement is usually observed within 48 hours.

Pediatric Patients 2 to 12 Years of Age : In pediatric patients 2 to 5 years of age (20 kg or less), the non-prescription liquid formulation of loperamide (1 mg/5 mL) should be used; for ages 6-12, either loperamide hydrochloride capsules or the non-prescription liquid formulation of loperamide may be used. For pediatric patients 2 to 12 years of age, the following schedule for capsules or liquid will usually fulfill initial dosage requirements:

Recommended First Day Dosage Schedule

Two to five years (13 to 20 kg): 1 mg three times daily (3 mg total daily dosage) Six to eight years (20 to 30 kg): 2 mg twice daily. (4 mg total daily dosage)

Eight to twelve years (greater than 30kg): 2 mg three times daily (6 mg total daily dosage)

Recommended Subsequent Daily Dosage

Following the first treatment day, it is recommended that subsequent Loperamide Hydrochloride Capsules doses (1 mg/10 kg body weight) be administered only after a loose stool. The total daily dosage should not exceed recommended dosages for the first day.

Chronic Diarrhea

Adults

'The recommended initial dose is 4 mg (two capsules) followed by 2 mg (one capsule) after each unformed stool until diarrhea is controlled, after which the dosage of Loperamide Hydrochloride Capsules should be reduced to meet individual requirements. When the optimal daily dosage has been established, this amount may then be administered as a single dose or in divided doses. The average daily maintenance dosage in clinical trials was 4 to 8 mg (two to four capsules per day). The maximum daily dosage is 16 mg (eight capsules per day). If clinical improvement is not observed after treatment with 16 mg per day for at least 10 days, symptoms are unlikely to be controlled by further administration. Loperamide Hydrochloride Capsules administration may be continued if diarrhea cannot be adequately controlled with diet or specific treatment.

Elderly

No formal pharmacokinetic studies were conducted in elderly subjects. However, there were no major differences reported in the drug disposition in elderly patients with diarrhea relative to young patients. No dose adjustment is required for the elderly.

In general, elderly patients may be more susceptible to drug-associated effects of the QT interval. Avoid Loperamide Hydrochloride Capsules in elderly patients taking drugs that can result in prolongation of the QT interval (for example, Class IA or III antiarrhythmics) or in patients with risk factors for Torsades de Pointes (see WARNINGS).

Renal Impairment

No pharmacokinetic data are available in patients with renal impairment. Since the metabolites and the unchanged drug are mainly excreted in the feces, no dosage adjustment is required for patients with renal impairment (see PRECAUTIONS).

Hepatic Impairment

The pharmacokinetics of loperamide have not been studied in patients with hepatic impairment.

Use Loperamide Hydrochloride Capsules with caution in such patients because the systemic exposure may be increased due to reduced metabolism (see PRECAUTIONS).

HOW SUPPLIED

Capsules - each capsule contains 2 mg of loperamide hydrochloride. The capsules have a light brown opaque cap and a light brown opaque body with an “^" over “605” imprinted radially on one segment.

NDC 51407-999-01

(100 CAPSULES)

NDC 51407-999-05

(500 CAPSULES)

Store at 20° to 25°C (68° to 77°F) [See USP Controlled Room Temperature].

Revised October 2021

Edenbridge Pharmaceuticals, LLC

Parsippany, NJ 07054

877-381-3336

Rx Only

Printed in USA

Marketed by:
GSMS, Inc.
Camarillo, CA 93012 USA